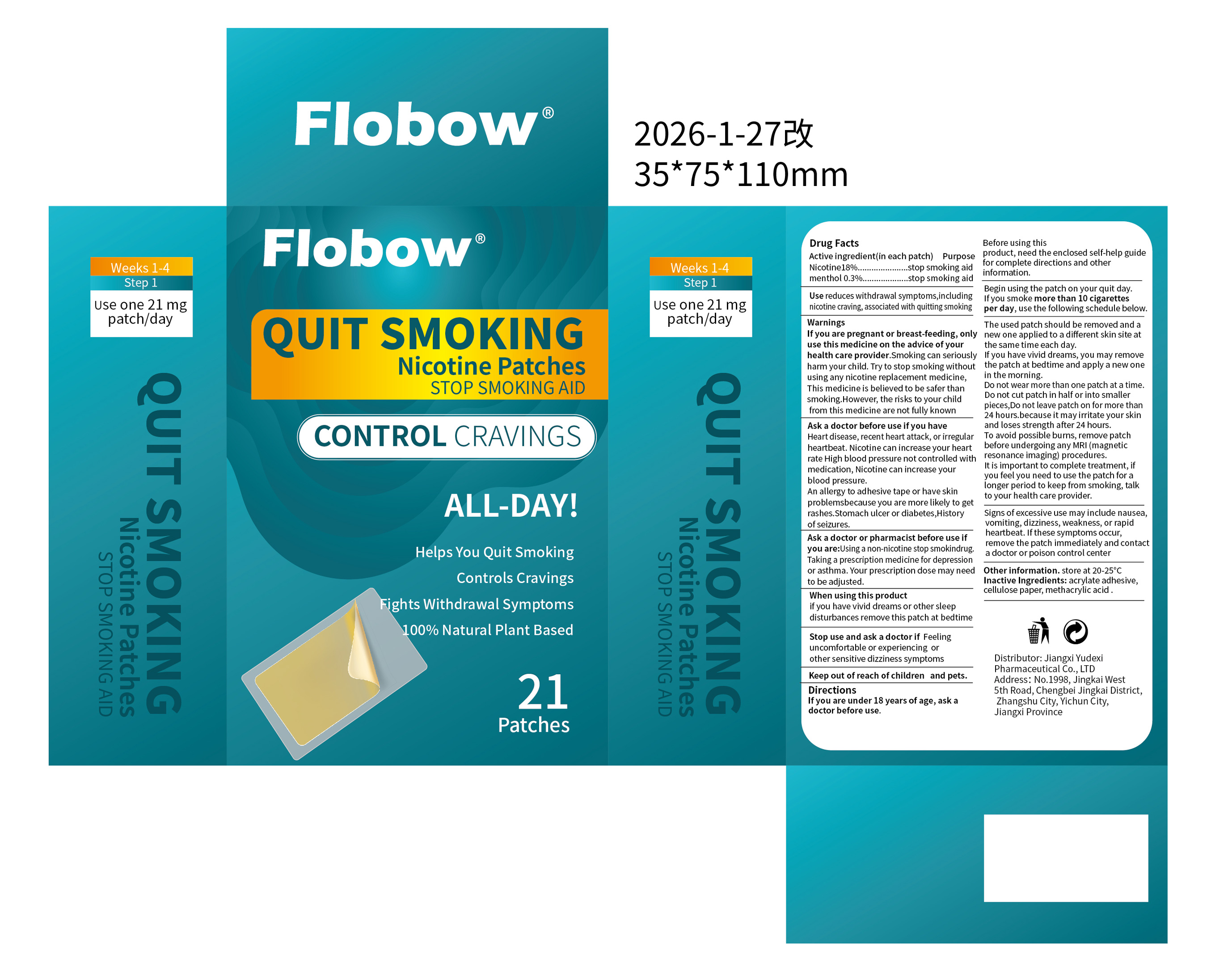 DRUG LABEL: Flobow  QUIT SMOKING Nicotine
NDC: 85248-012 | Form: PATCH
Manufacturer: Jiangxi Yudexi Pharmaceutical Co., LTD
Category: otc | Type: HUMAN OTC DRUG LABEL
Date: 20260127

ACTIVE INGREDIENTS: NICOTINE 18 g/100 1; MENTHOL 0.3 g/100 1
INACTIVE INGREDIENTS: 2-HYDROXYETHYL ACRYLATE; METHACRYLIC ACID; POWDERED CELLULOSE

85248-012

Active Ingredient

Nicotine 18%.menthol 0.3%

Purpose

stop smoking aid

Use

reduces withdrawal symptoms,including nicotine craving,associated with quitting smoking

Warnings

If you are pregnant or breast-feeding, only use this medicine on the advice of your health care provider.Smoking can seriously harm your child. Try to stop smoking without using any nicotine replacement medicine,This medicine is believed to be safer than smoking.However, the risks to your child from this medicine are not fully known

Do not use

Do not wear more than one patch at a time.Do not cut patch in half or into smaller pieces,Do not leave patch on for more than 24 hours.because it may irritate your skin and loses strength after 24 hours.To avoid possible burns, remove patch before undergoing any MRl (magnetic resonance imaging)procedures.It is important to complete treatment,if you feel you need to use the patch for a longer period to keep from smoking, talk to your health care provider.

When Using

if you have vivid dreams or other sleep disturbances remove this patch at bedtime

Stop Use

Stop use and ask a doctor if Feeling uncomfortable or experiencing or other sensitive dizziness symptoms

Ask Doctor

Ask a doctor before use if you have
Heart disease, recent heart attack, or irregular heartbeat. Nicotine can increase your heart rate. High blood pressure not controlled with medication. Nicotine can increase your blood pressure.
An allergy to adhesive tape or have skin problems because you are more likely to get rashes. Stomach ulcer or diabetes, History of seizures.
Ask a doctor or pharmacist before use if you are: Using a non-nicotine stop smoking drug.
Taking a prescription medicine for depression or asthma. Your prescription dose may need to be adjusted.

Keep Oot Of Reach Of Children

Keep out ofreach of children and pets.

Directions

If you are under 18 years of age, ask adoctor before use. Before using this product,need the enclosed self-help guide for complete directions and other information. Begin using the patch on your quit day.If you smoke more than 10 cigarettes per day, use the following schedule below. The used patch should be removed and a new one applied to a different skin site at the same time each day.If you have vivid dreams, you may removethe patch at bedtime and apply a new one in the morning.Do not wear more than one patch at a time.Do not cut patch in half or into smaller pieces,Do not leave patch on for more than 24 hours.because it may irritate your skin and loses strength after 24 hours.To avoid possible burns, remove patch before undergoing any MRl (magnetic resonance imaging)procedures.It is important to complete treatment,if you feel you need to use the patch for a longer period to keep from smoking, talk to your health care provider. Signs of excessive use may include nausea.vomiting,dizziness,weakness, or rapid heartbeat.lf these symptoms occur,remove the patch immediately and contact a doctor or poison control center

Other information

store at 20-25°C

Inactive ingredients

acrylate adhesive，cellulose paper，methacrylic acid .